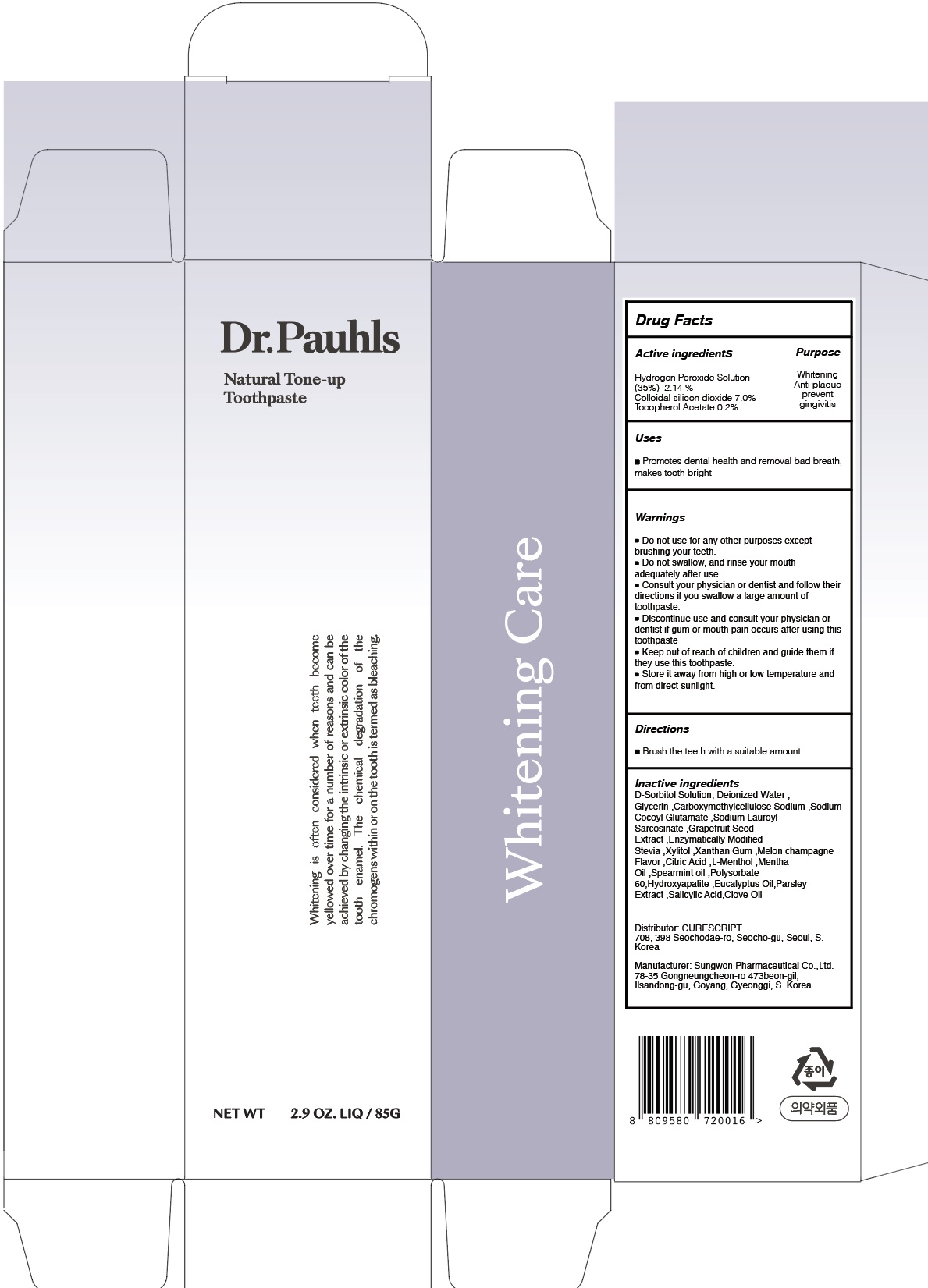 DRUG LABEL: DR.PAUHLS NATURAL TONE UP TOOTH
NDC: 72265-100 | Form: PASTE, DENTIFRICE
Manufacturer: CURESCRIPT
Category: otc | Type: HUMAN OTC DRUG LABEL
Date: 20210209

ACTIVE INGREDIENTS: HYDROGEN PEROXIDE 1.81 g/85 g; SILICON DIOXIDE 5.95 g/85 g; .ALPHA.-TOCOPHEROL ACETATE 0.17 g/85 g
INACTIVE INGREDIENTS: SORBITOL; Water; Glycerin

ACTIVE INGREDIENTS

Hydrogen Peroxide Solution (35%) 2.14 %
Colloidal silicon dioxide 7.0%
Tocopherol Acetate 0.2%

INACTIVE INGREDIENTS

D-Sorbitol Solution, Deionized Water , Glycerin ,Carboxymethylcellulose Sodium ,Sodium Cocoyl Glutamate ,Sodium Lauroyl Sarcosinate ,Grapefruit Seed Extract ,Enzymatically Modified Stevia ,Xylitol ,Xanthan Gum ,Melon champagne Flavor ,Citric Acid ,L-Menthol ,Mentha Oil ,Spearmint oil ,Polysorbate 60,Hydroxyapatite ,Eucalyptus Oil,Parsley Extract ,Salicylic Acid,Clove Oil

PURPOSE

Whitening
Anti plaque
prevent gingivitis

WARNINGS

■ Do not use for any other purposes except brushing your teeth.
■ Do not swallow, and rinse your mouth adequately after use.
■ Consult your physician or dentist and follow their directions if you swallow a large amount of toothpaste.
■ Discontinue use and consult your physician or dentist if gum or mouth pain occurs after using this toothpaste
■ Keep out of reach of children and guide them if they use this toothpaste.
■ Store it away from high or low temperature and from direct sunlight.

■ Keep out of reach of children and guide them if they use this toothpaste.

Uses

■ Promotes dental health and removal bad breath, makes tooth bright

Directions

■ Brush the teeth with a suitable amount.